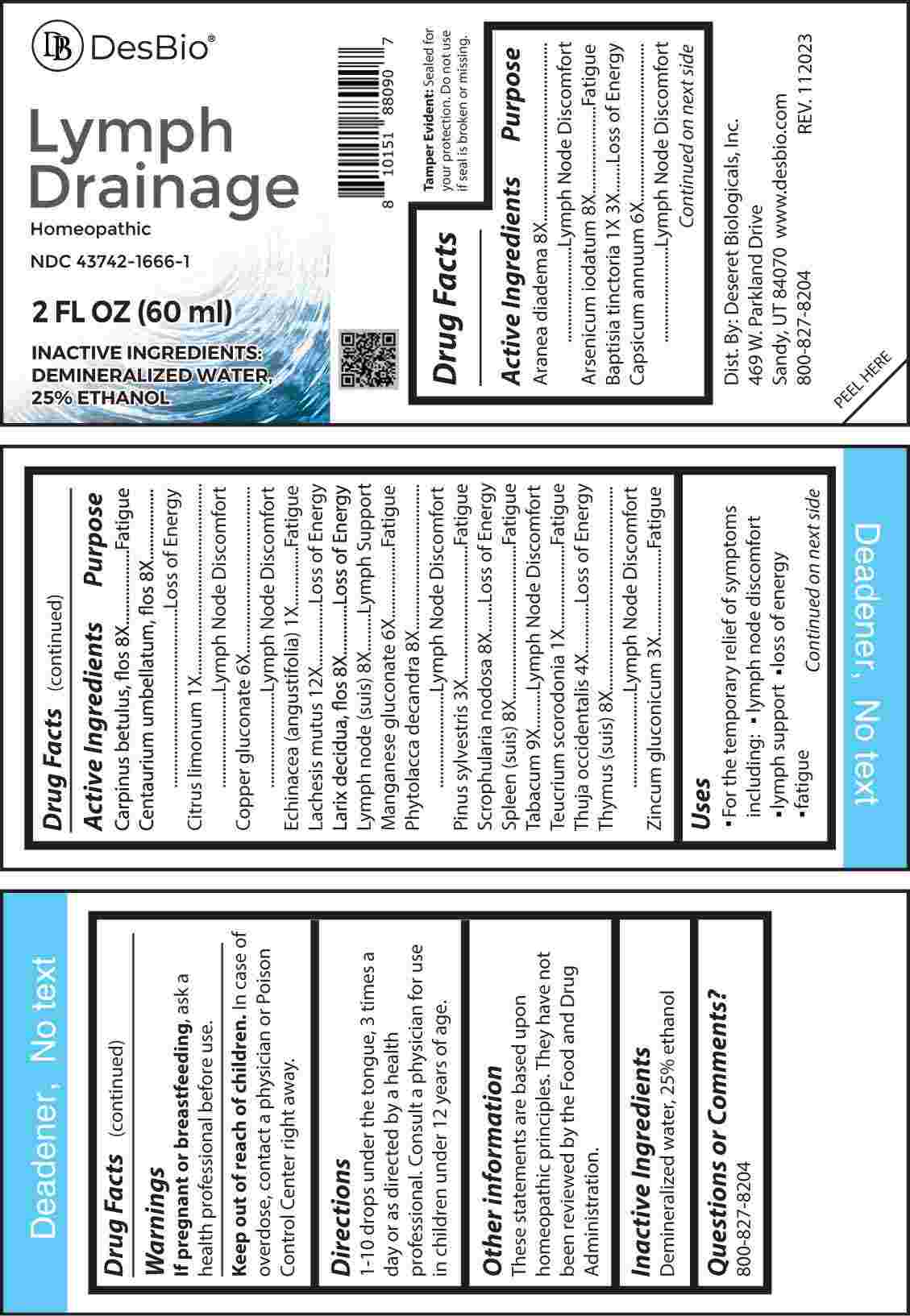 DRUG LABEL: Lymph Drainage
NDC: 43742-1666 | Form: LIQUID
Manufacturer: Deseret Biologicals
Category: homeopathic | Type: HUMAN OTC DRUG LABEL
Date: 20240216

ACTIVE INGREDIENTS: LEMON JUICE 1 [hp_X]/1 mL; ECHINACEA ANGUSTIFOLIA WHOLE 1 [hp_X]/1 mL; TEUCRIUM SCORODONIA FLOWERING TOP 1 [hp_X]/1 mL; BAPTISIA TINCTORIA ROOT 1 [hp_X]/1 mL; PINUS SYLVESTRIS LEAFY TWIG 3 [hp_X]/1 mL; ZINC GLUCONATE 3 [hp_X]/1 mL; THUJA OCCIDENTALIS LEAFY TWIG 4 [hp_X]/1 mL; CAPSICUM 6 [hp_X]/1 mL; COPPER GLUCONATE 6 [hp_X]/1 mL; MANGANESE GLUCONATE 6 [hp_X]/1 mL; ARANEUS DIADEMATUS 8 [hp_X]/1 mL; ARSENIC TRIIODIDE 8 [hp_X]/1 mL; CARPINUS BETULUS FLOWERING TOP 8 [hp_X]/1 mL; CENTAURIUM ERYTHRAEA FLOWER 8 [hp_X]/1 mL; LARIX DECIDUA FLOWERING TOP 8 [hp_X]/1 mL; SUS SCROFA LYMPH 8 [hp_X]/1 mL; PHYTOLACCA AMERICANA ROOT 8 [hp_X]/1 mL; SCROPHULARIA NODOSA WHOLE 8 [hp_X]/1 mL; SUS SCROFA SPLEEN 8 [hp_X]/1 mL; SUS SCROFA THYMUS 8 [hp_X]/1 mL; TOBACCO LEAF 9 [hp_X]/1 mL; LACHESIS MUTA VENOM 12 [hp_X]/1 mL
INACTIVE INGREDIENTS: WATER; ALCOHOL

DRUG FACTS:

ACTIVE INGREDIENTS:

Aranea Diadema 8X, Arsenicum Iodatum 8X, Baptisia Tinctoria 1X, 3X, Capsicum Annuum 6X, Carpinus Betulus, Flos 8X, Centaurium Umbellatum, Flos 8X, Citrus Limonum 1X, Copper Gluconate 6X, Echinacea (Angustifolia) 1X, Lachesis Mutus 12X, Larix Decidua, Flos 8X, Lymph Node (Suis) 8X, Manganese Gluconate 6X, Phytolacca Decandra 8X, Pinus Sylvestris 3X, Scrophularia Nodosa 8X, Spleen (Suis) 8X, Tabacum 9X, Teucrium Scorodonia 1X, Thuja Occidentalis 4X, Thymus (Suis) 8X, Zincum Gluconicum 3X.

PURPOSE:

Aranea Diadema – Lymph Node Discomfort, Arsenicum Iodatum - Fatigue, Baptisia Tinctoria – Loss of Energy, Capsicum Annuum – Lymph Node Discomfort, Carpinus Betulus, Flos - Fatigue, Centaurium Umbellatum, Flos – Loss of Energy, Citrus Limonum – Lymph Node Discomfort, Copper Gluconate – Lymph Node Discomfort, Echinacea (Angustifolia) - Fatigue, Lachesis Mutus – Loss of Energy, Larix Decidua, Flos – Loss of Energy, Lymph Node (Suis) – Lymph Support, Manganese Gluconate - Fatigue, Phytolacca Decandra – Lymph Node Discomfort, Pinus Sylvestris - Fatigue, Scrophularia Nodosa – Loss of Energy, Spleen (Suis) - Fatigue, Tabacum – Lymph Node Discomfort, Teucrium Scorodonia - Fatigue, Thuja Occidentalis – Loss of Energy, Thymus (Suis) – Lymph Node Discomfort, Zincum Gluconicum - Fatigue.

USES:

• For the temporary relief of symptoms including:

• lymph node discomfort • lymph support

• loss of energy • fatigue

These statements are based upon homeopathic principles. They have not been reviewed by the Food and Drug Administration.

WARNINGS:

If pregnant or breast-feeding, ask a health professional before use.

Keep out of reach of children. In case of overdose, contact a physician or Poison Control Center right away.

Tamper Evident: Sealed for your protection. Do not use if seal is broken or missing.

KEEP OUT OF REACH OF CHILDREN:

In case of overdose, contact a physician or Poison Control Center right away.

DIRECTIONS:

1-10 drops under the tongue, 3 times a day or as directed by a health professional. Consult a physician for use in children under 12 years of age.

INACTIVE INGREDIENTS:

Demineralized water, 25% ethanol

QUESTIONS:

Dist. By: Deseret Biologicals, Inc.
469 W. Parkland Drive
Sandy, UT 84070 www.desbio.com

800-827-8204

PACKAGE LABEL DISPLAY:

Des Bio

Lymph

Drainage

Homeopathic

NDC 43742-1666-1

2 FL OZ (60 ml)